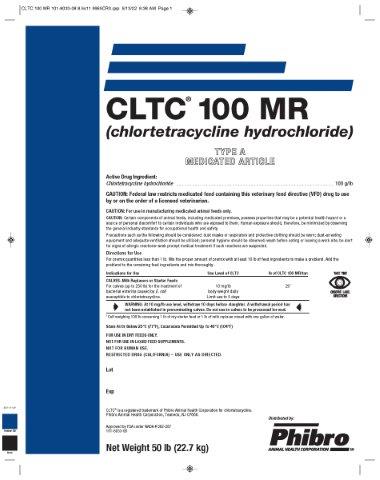 DRUG LABEL: CLTC 100 MR
NDC: 66104-6300 | Form: POWDER
Manufacturer: Phibro Animal Health
Category: animal | Type: VFD TYPE A MEDICATED ARTICLE ANIMAL DRUG LABEL
Date: 20230720

ACTIVE INGREDIENTS: CHLORTETRACYCLINE HYDROCHLORIDE 100 g/0.45 kg
INACTIVE INGREDIENTS: DEXTROSE, UNSPECIFIED FORM

CLTC® 100 MR
(chlortetracycline hydrochloride)
TYPE A MEDICATED ARTICLE

Active Drug Ingredient:

Chlortetracycline hydrochloride . . . . . . . . . . .. . . . . . . . . . . . . . . . . . . . . . . . . . . . . . . . 100 g/lb

CAUTION:

CAUTION: Federal law restricts medicated feed containing this veterinary feed directive (VFD) drug to use by or on the order of a licensed veterinarian.

For use in manufacturing medicated animal feeds only.

CAUTION: Certain components of animal feeds, including medicated premixes, possess properties that may be a potential health hazard or a source of personal discomfort to certain individuals who are exposed to them. Human exposure should, therefore, be minimized by observing the general industry standards for occupational health and safety.

Precautions such as the following should be considered: dust masks or respirators and protective clothing should be worn; dust-arresting equipment and adequate ventilation should be utilized; personal hygiene should be observed; wash before eating or leaving a work site; be alert for signs of allergic reactions–seek prompt medical treatment if such reactions are suspected.

Directions for Use

For premix quantities less than 1 lb. Mix the proper amount of premix with at least 10 lb of feed ingredients to make a preblend. Add the preblend to the remaining feed ingredients and mix thoroughly.

Indications for Use

Use Level of CLTC

lb of CLTC 100 MR/ton

CALVES–Milk Replacers or Starter Feeds For calves (up to 250 lb) for the treatment of bacterial enteritis caused by E. coli susceptible to chlortetracycline.

10 mg/lb

body weight daily

Limit use to 5 days

20^1

WARNING: At 10 mg/lb use level, withdraw 10 days before slaughter. A withdrawal period has not been established in preruminating calves. Do not use in calves to be processed for veal.

^1 Calf weighing 100 lb consuming 1 lb of dry starter feed or 1 lb of milk replacer mixed with one gallon of water.

INDICATIONS AND USAGE

FOR USE IN DRY FEEDS ONLY.

NOT FOR USE IN LIQUID FEED SUPPLEMENTS.

NOT FOR HUMAN USE.

RESTRICTED DRUG (CALIFORNIA) – USE ONLY AS DIRECTED.

CLTC® is a registered trademark of Phibro Animal Health Corporation for chlortetracycline.

Phibro Animal Health Corporation, Teaneck, NJ 07660.

Net Weight 50 lb (22.7 kg)

Approved by FDA under NADA # 092-287

101-8033-08